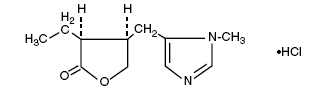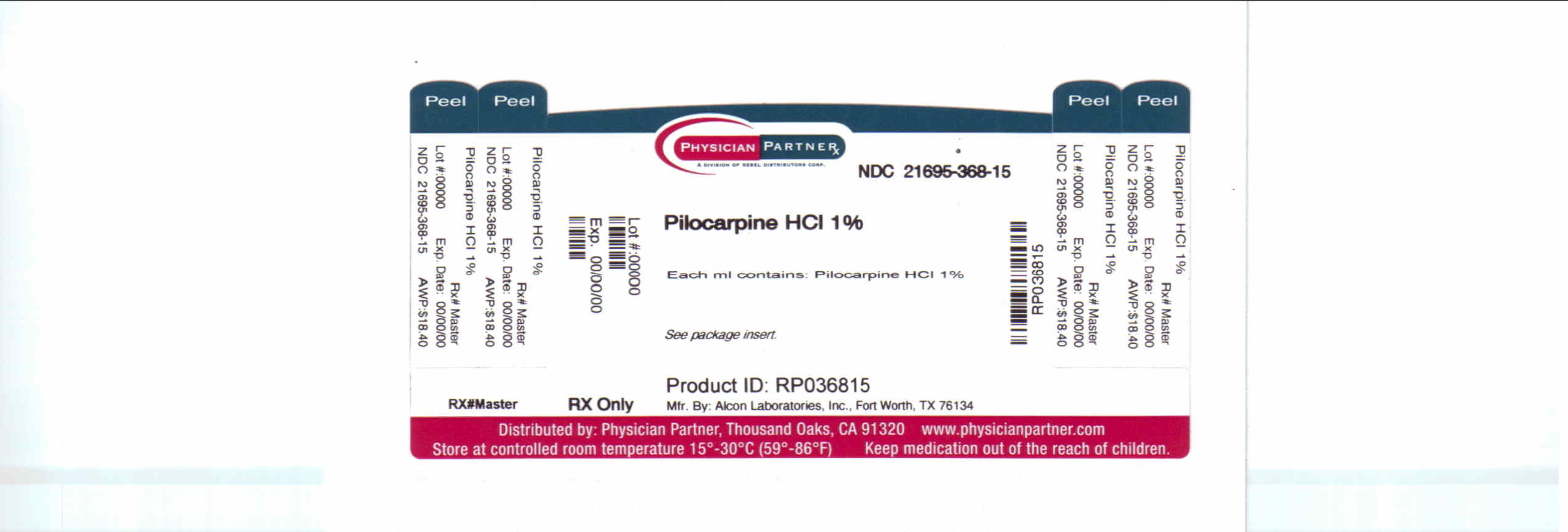 DRUG LABEL: PILOCARPINE HYDROCHLORIDE
NDC: 21695-368 | Form: SOLUTION/ DROPS
Manufacturer: Rebel Distributors Corp
Category: prescription | Type: HUMAN PRESCRIPTION DRUG LABEL
Date: 20110315

ACTIVE INGREDIENTS: PILOCARPINE HYDROCHLORIDE 10 mg/1 mL
INACTIVE INGREDIENTS: HYPROMELLOSES; WATER; SODIUM HYDROXIDE; HYDROCHLORIC ACID; BENZALKONIUM CHLORIDE; BORIC ACID; SODIUM CITRATE; SODIUM CHLORIDE

Pilocarpine Hydrochloride Ophthalmic Solution USP (Sterile)

Rx only

DESCRIPTION:

Pilocarpine Hydrochloride is a cholinergic prepared as a sterile topical ophthalmic solution. The active ingredient is represented by the chemical structural formula:

C11H16N2O2•HCl

Mol. Wt. 244.72

2(3H)-Furanone, 3-ethyldihydro-4-[(1-methyl-1H-imidazol-5-yl)methyl] - monohydrochloride, [3S-cis] -

Pilocarpine HCI 0.5%

EACH mL CONTAINS: ACTIVE: Pilocarpine Hydrochloride 10 mg (1%); INACTIVES: Hypromellose, boric acid, sodium citrate, sodium chloride, Purified Water. Sodium Hydroxide (added to adjust pH).
PRESERVATIVE ADDED: Benzalkonium Chloride 0.01%.

Pilocarpine HCI 4%

EACH mL CONTAINS: ACTIVE: Pilocarpine Hydrochloride 40 mg (4%); INACTIVES: Hypromellose, Monobasic Sodium Phosphate, Edetate Disodium, Dibasic Sodium Phosphate, Purified Water. Sodium Hydroxide and/or Hydrochloric Acid may be added to adjust pH (3.5 - 5.5). PRESERVATIVE ADDED: Benzalkonium Chloride 0.01%.

CLINICAL PHARMACOLOGY:

The actions of pilocarpine hydrochloride are those of pilocarpine, a cholinergic substance. Its penetration, following topical application to the eye, results in parasympathomimetic reactions by responsive tissues.

INDICATIONS AND USAGE:

Pilocarpine hydrochloride can be used in the medical management of glaucoma, especially open-angle glaucoma, in those cases in which the intraocular pressure can be controlled adequately by the topical administration of pilocarpine. In acute (closed-angle) glaucoma, pilocarpine hydrochloride may be used alone, or in combination with other cholinergic agents or carbonic anhydrase inhibitors, to relieve tension prior to emergency surgery.

Patients may be maintained on pilocarpine hydrochloride as long as intraocular pressure is controlled and there is no deterioration in the visual fields. The choice of concentration should be determined by the severity of the condition and the response of the patient. Pilocarpine hydrochloride is also indicated to counter the effects of cycloplegics and mydriatics following surgery or ophthalmoscopic examination.

CONTRAINDICATIONS:

Parasympathomimetics are contraindicated where miosis is undesirable such as acute iritis or pupillary block glaucoma.

This product is also contraindicated in persons hypersensitive to one or more of the components of this preparation.

WARNINGS:

Not for internal use. To prevent contaminating the dropper tip and solution, care should be taken not to touch the eyelids or surrounding areas with the dropper tip of the bottle.

PRECAUTIONS:

This pilocarpine-induced miosis may cause difficulty in dark adaptation. The patient should exercise caution when involved in night driving or other hazardous activities in poor light.

Carcinogenesis, Mutagenesis, Impairment of Fertility:

There have been no long-term studies done using pilocarpine in animals to evaluate carcinogenic potential.

Pregnancy Category C:

Animal studies have not been conducted with pilocarpine. It is also not known whether pilocarpine can cause fetal harm when administered to a pregnant women or can affect reproduction capacity. Pilocarpine should be given to a pregnant women only if clearly needed.

Nursing Mothers:

It is not known whether the drug is excreted in human milk. Because many drugs are excreted in human milk, caution should be exercised when pilocarpine is administered to a nursing woman.

ADVERSE REACTIONS:

OCULAR: Transient symptoms of stinging and burning may occur. Ciliary spasm, conjunctival vascular congestion, temporal or supraorbital headache, lacrimation and induced myopia may occur. This is especially true in younger individuals who have recently started administration. Reduced visual acuity in poor illumination is frequently experienced by older individuals and individuals with lens opacity. Miotic agents may also cause retinal detachment; thus, care should be exercised with all miotic therapy especially in young myopic patients. Lens opacity may occur with prolonged use of pilocarpine.

SYSTEMIC: Systemic reactions following topical administration, although extremely rare, have included hypertension, tachycardia, bronchiolar spasm, pulmonary edema, salivation, sweating, nausea, vomiting, and diarrhea.

DOSAGE AND ADMINISTRATION:

The initial dose is one or two drops in the affected eye(s). This may be repeated up to three or four times daily or as directed by a physician. The frequency of instillation and concentration of pilocarpine hydrochloride ophthalmic solution are determined by the severity of the glaucoma and miotic response of the patient. Individuals with heavily pigmented irides may require higher strengths.

During acute phases, the miotic must be instilled into the unaffected eye to prevent an attack of angle-closure glaucoma.

DO NOT USE IF IMPRINTED NECKBAND IS NOT INTACT.

HOW SUPPLIED

Pilocarpine Hydrochloride Ophthalmic Solution USP is supplied in 15 ml plastic DROP-TAINER* dispensers.

BOXED WARNING

Pilocarpine HCl Ophthalmic Solution USP, 1%
15 mL - NDC 21695-368-01

*DROP-TAINER is a registered trademark of Alcon Manufacturing Ltd.

NOT FOR INJECTION.

FOR OPHTHALMIC USE ONLY.

STORAGE: Store between 8°- 27°C (46°- 80°F).

KEEP OUT OF REACH OF CHILDREN.

Manufactured by: ALCON LABORATORIES, INC, Fort Worth, TX 76134

Distributed by: FALCON PHARMACEUTICALS LTD., Fort Worth, TX 76134

Repackaged by: REBEL DISTRIBUTORS CORP, Thousand Oaks, CA 91320